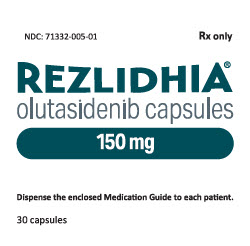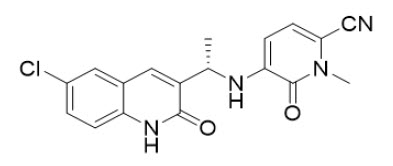 DRUG LABEL: REZLIDHIA
NDC: 71332-005 | Form: CAPSULE
Manufacturer: Rigel Pharmaceuticals, Inc.
Category: prescription | Type: HUMAN PRESCRIPTION DRUG LABEL
Date: 20251105

ACTIVE INGREDIENTS: OLUTASIDENIB 150 mg/1 1
INACTIVE INGREDIENTS: CROSCARMELLOSE SODIUM; MAGNESIUM STEARATE; MICROCRYSTALLINE CELLULOSE; GELATIN, UNSPECIFIED; TITANIUM DIOXIDE; FERROSOFERRIC OXIDE; PROPYLENE GLYCOL; SHELLAC

HIGHLIGHTS OF PRESCRIBING INFORMATION

These highlights do not include all the information needed to use REZLIDHIA safely and effectively. See full prescribing information for REZLIDHIA.
REZLIDHIA® (olutasidenib) capsules, for oral use
Initial U.S. Approval: 2022

WARNING: DIFFERENTIATION SYNDROME

See full prescribing information for complete boxed warning.

- Differentiation syndrome, which can be fatal, can occur with REZLIDHIA treatment.
- If differentiation syndrome is suspected, withhold REZLIDHIA and initiate corticosteroids and hemodynamic monitoring until symptom resolution. (5.1)

1 INDICATIONS AND USAGE

REZLIDHIA is an isocitrate dehydrogenase-1 (IDH1) inhibitor indicated for the treatment of adult patients with relapsed or refractory acute myeloid leukemia (AML) with a susceptible IDH1 mutation as detected by an FDA-approved test. (1)

2 DOSAGE AND ADMINISTRATION

Select patients based on presence of IDH1 mutation(s). (2.1)

- Recommended dosage: 150 mg orally twice daily, until disease progression or unacceptable toxicity. (2.2)
- Take on an empty stomach at least 1 hour before or 2 hours after a meal. (2.2)

3 DOSAGE FORMS AND STRENGTHS

Capsules: 150 mg (3)

4 CONTRAINDICATIONS

None. (4)

5 WARNINGS AND PRECAUTIONS

- Hepatotoxicity: Monitor liver function tests during treatment with REZLIDHIA. If hepatotoxicity occurs, interrupt and reduce or discontinue REZLIDHIA. (2.3, 5.2)

6 ADVERSE REACTIONS

The most common (≥20%) adverse reactions, including laboratory abnormalities, are aspartate aminotransferase increased, alanine aminotransferase increased, potassium decreased, sodium decreased, alkaline phosphatase increased, nausea, creatinine increased, fatigue/malaise, arthralgia, constipation, lymphocytes increased, bilirubin increased, leukocytosis, uric acid increased, dyspnea, pyrexia, rash, lipase increased, mucositis, diarrhea and transaminitis. (6.1)

To report SUSPECTED ADVERSE REACTIONS, contact Rigel Pharmaceuticals, Inc. at 1-800-983-1329 or FDA at 1-800-FDA-1088 or www.fda.gov/medwatch.

7 DRUG INTERACTIONS

- Strong or moderate CYP3A Inducers: Avoid concomitant use. (7.1)
- Sensitive CYP3A Substrates: Avoid concomitant use. Monitor if unavoidable. (7.1)

8 USE IN SPECIFIC POPULATIONS

Lactation: Advise not to breastfeed. (8.2)

FULL PRESCRIBING INFORMATION

WARNING: DIFFERENTIATION SYNDROME

Differentiation syndrome, which can be fatal, can occur with REZLIDHIA treatment. Symptoms may include dyspnea, pulmonary infiltrates/pleuropericardial effusion, kidney injury, hypotension, fever, and weight gain.

If differentiation syndrome is suspected, withhold REZLIDHIA and initiate treatment with corticosteroids and hemodynamic monitoring until symptom resolution [see Warnings and Precautions (5.1)].

1 INDICATIONS AND USAGE

Relapsed or Refractory Acute Myeloid Leukemia

REZLIDHIA is indicated for the treatment of adult patients with relapsed or refractory acute myeloid leukemia (AML) with a susceptible isocitrate dehydrogenase-1 (IDH1) mutation as detected by an FDA-approved test [see Dosage and Administration (2.1), Clinical Pharmacology (12.1), and Clinical Studies (14.1)].

2 DOSAGE AND ADMINISTRATION

2.1 Patient Selection

Select patients for the treatment of relapsed or refractory AML with REZLIDHIA based on the presence of IDH1 mutations in blood or bone marrow [see Clinical Trials (14.1)]. Information on FDA- approved tests for the detection of IDH1 mutations in AML is available at http://www.fda.gov/CompanionDiagnostics.

2.2 Recommended Dosage

The recommended dosage of REZLIDHIA is 150 mg taken orally twice daily until disease progression or unacceptable toxicity. Administer REZLIDHIA capsules orally about the same time each day. Do not administer 2 doses within 8 hours. Take on an empty stomach at least 1 hour before or 2 hours after a meal [see Clinical Pharmacology (12.3)]. For patients without disease progression or unacceptable toxicity, treat for a minimum of 6 months to allow time for clinical response.

Swallow REZLIDHIA capsules whole. Do not break, open, or chew the capsules. If a dose of REZLIDHIA is vomited, do not administer a replacement dose; wait until the next scheduled dose is due. If a dose of REZLIDHIA is missed or not taken at the usual time, administer the dose as soon as possible and at least 8 hours prior to the next scheduled dose. Return to the normal schedule the following day.

2.3 Monitoring and Dosage Modifications for Adverse Reactions

Assess blood counts, and blood chemistries including liver function tests prior to initiation of REZLIDHIA, at least once weekly for the first two months; once every other week for the third month; once in the fourth month, and once every other month for the duration of therapy. Manage any abnormalities promptly [see Warnings and Precautions (5.1 and 5.2) and Adverse Reactions (6.1)].

Interrupt dosing or reduce dose for toxicities. See Table 1 for dosage modification guidelines.

Table 1: Recommended Dosage Modifications for REZLIDHIA
Adverse Reactions | Recommended Action
Differentiation Syndrome [see Warnings and Precautions (5.1)] | - If differentiation syndrome is suspected, withhold REZLIDHIA until signs and symptoms improve. - Administer systemic corticosteroids and initiate hemodynamic monitoring until symptom resolution and for a minimum of 3 days. - Resume REZLIDHIA at 150 mg twice daily after resolution of differentiation syndrome. - If a recurrence of differentiation syndrome is suspected, withhold REZLIDHIA and institute treatment per above guidance. After resolution of symptoms, REZLIDHIA may be resumed at a reduced dose of 150 mg once daily for a minimum of 7 days, after which it can be increased to 150 mg twice daily.
Noninfectious leukocytosis [see Adverse Reactions (6.1)] | - Initiate treatment with hydroxyurea, as per standard practices. Taper hydroxyurea only after leukocytosis improves or resolves.
Grade 3 [Grade 1 is mild, Grade 2 is moderate, Grade 3 is severe, Grade 4 is life-threatening. Severity as defined by National Cancer Institute Common Terminology Criteria for Adverse Events (NCI CTCAE version 4.03).] hepatotoxicity [see Warnings and Precautions (5.2)] | - Withhold REZLIDHIA and monitor liver function tests, twice per week, until laboratory values have returned to baseline or Grade 1 toxicity. - Resume REZLIDHIA at a reduced dose of 150 mg once daily and continue monitoring; may increase to 150 mg twice daily if hepatotoxicity resolves to baseline for at least 28 days. - If hepatotoxicity (Grade 3) recurs at 150 mg once daily, discontinue REZLIDHIA.
Grade 4 hepatotoxicity or AST or ALT >3x ULN and total bilirubin >2x ULN and alkaline phosphatase <2x ULN in the absence of a clear alternative explanation [see Warnings and Precautions (5.2)] | - Permanently discontinue REZLIDHIA
Other Grade 3 or higher toxicity considered related to treatment [see Adverse Reactions (6.1)] | - Interrupt REZLIDHIA until toxicity resolves to Grade 2 or lower. - Resume REZLIDHIA at 150 mg once daily; may increase to 150 mg twice daily if toxicities resolve to Grade 1 or lower for at least 1 week. - If Grade 3 or higher toxicity recurs at 150 mg once daily, discontinue REZLIDHIA.

3 DOSAGE FORMS AND STRENGTHS

Capsules: 150 mg opaque white capsules imprinted with "OLU 150".

4 CONTRAINDICATIONS

None.

5 WARNINGS AND PRECAUTIONS

5.1 Differentiation Syndrome

REZLIDHIA can cause differentiation syndrome. In the clinical trial of REZLIDHIA in patients with relapsed or refractory AML, differentiation syndrome occurred in 16% (25/153) of patients, with grade 3 or 4 differentiation syndrome occurring in 8% of patients treated, and fatalities in 1% of patients [see Adverse Reactions (6.1)]. Differentiation syndrome is associated with rapid proliferation and differentiation of myeloid cells and may be life-threatening or fatal. Symptoms of differentiation syndrome in patients treated with REZLIDHIA included leukocytosis, dyspnea, pulmonary infiltrates/pleuropericardial effusion, kidney injury, fever, edema, pyrexia, and weight gain. Of the 25 patients who experienced differentiation syndrome, 19 (76%) recovered after treatment or after dosage interruption of REZLIDHIA. Differentiation syndrome occurred as early as 1 day and up to 18 months after REZLIDHIA initiation and has been observed with or without concomitant leukocytosis.

If differentiation syndrome is suspected, temporarily withhold REZLIDHIA and initiate systemic corticosteroids (e.g., dexamethasone 10 mg IV every 12 hours) for a minimum of 3 days and until resolution of signs and symptoms. If concomitant leukocytosis is observed, initiate treatment with hydroxyurea, as clinically indicated. Taper corticosteroids and hydroxyurea after resolution of symptoms. Differentiation syndrome may recur with premature discontinuation of corticosteroids and/or hydroxyurea treatment. Institute supportive measures and hemodynamic monitoring until improvement; withhold dose of REZLIDHIA and consider dose reduction based on recurrence [see Dosage and Administration (2.3)].

5.2 Hepatotoxicity

REZLIDHIA can cause hepatotoxicity, presenting as increased alanine aminotransferase (ALT), increased aspartate aminotransferase (AST), increased blood alkaline phosphatase, and/or elevated bilirubin. Of 153 patients with relapsed or refractory AML who received REZLIDHIA, hepatotoxicity occurred in 23% of patients; 13% experienced grade 3 or 4 hepatotoxicity [see Adverse Reactions (6.1)]. One patient treated with REZLIDHIA in combination with azacitidine in the clinical trial, a combination for which REZLIDHIA is not indicated, died from complications of drug-induced liver injury. The median time to onset of hepatotoxicity in patients with relapsed or refractory AML treated with REZLIDHIA was 1.2 months (range: 1 day to 17.5 months) after REZLIDHIA initiation, and the median time to resolution was 12 days (range: 1 day to 17 months). The most common hepatotoxicities were elevations of ALT, AST, blood alkaline phosphatase, and blood bilirubin.

Monitor patients frequently for clinical symptoms of hepatic dysfunction such as fatigue, anorexia, right upper abdominal discomfort, dark urine, or jaundice. Obtain baseline liver function tests prior to initiation of REZLIDHIA, at least once weekly for the first two months, once every other week for the third month, once in the fourth month, and once every other month for the duration of therapy. If hepatic dysfunction occurs, withhold, reduce, or permanently discontinue REZLIDHIA based on recurrence/severity [see Dosage and Administration (2.3)].

6 ADVERSE REACTIONS

The following clinically significant adverse reactions are described elsewhere in the labeling:

- Differentiation Syndrome [see Warnings and Precautions (5.1)]
- Hepatotoxicity [see Warnings and Precautions (5.2)]

Because clinical trials are conducted under widely varying conditions, adverse reaction rates observed in the clinical trials of a drug cannot be directly compared to rates in the clinical trials of another drug and may not reflect the rates observed in practice.

6.1 Clinical Trials Experience

Relapsed or Refractory AML

The safety of REZLIDHIA 150 mg administered twice daily was evaluated in 153 adults with relapsed or refractory AML with an IDH1 mutation [see Clinical Studies (14.1)]. Among the 153 patients who received REZLIDHIA, 35% were exposed for at least 6 months and 21% were exposed for at least 1 year. The median duration of exposure to REZLIDHIA was 4.7 months (range: 0.1 to 34 months).

Serious adverse reactions occurred in 25% of patients who received REZLIDHIA. Serious adverse reactions in ≥5% included differentiation syndrome (9%) and transaminitis (6%). Fatal adverse reactions occurred in 1% of patients who received REZLIDHIA, due to differentiation syndrome.

Permanent discontinuation of REZLIDHIA due to an adverse reaction occurred in 8% of patients. Adverse reactions leading to permanent discontinuation in ≥1% of patients included transaminitis, differentiation syndrome, and gallbladder disorders.

Dosage interruptions of REZLIDHIA due to an adverse reaction occurred in 32% of patients. Adverse reactions which required dosage interruption in >5% of patients included transaminitis and differentiation syndrome.

Dose reductions of REZLIDHIA due to an adverse reaction occurred in 11% of patients. Adverse reactions which required dose reductions in ≥2% of patients included transaminitis.

The most common (≥20%) adverse reactions, including laboratory abnormalities, were aspartate aminotransferase increased, alanine aminotransferase increased, potassium decreased, sodium decreased, alkaline phosphatase increased, nausea, creatinine increased, fatigue/malaise, arthralgia, constipation, lymphocytes increased, bilirubin increased, leukocytosis, uric acid increased, dyspnea, pyrexia, rash, lipase increased, mucositis, diarrhea and transaminitis.

Table 2 summarizes the adverse reactions in the clinical trial for relapsed or refractory AML.

Table 2: Adverse Reactions (≥10%) in Patients with Relapsed or Refractory AML in the Clinical Trial
 | Olutasidenib 150 mg BID N=153
Body System Adverse Reaction | All Grades (%) | Grade 3 or 4 (%)
Gastrointestinal Disorders
Nausea | 38 | 0
Constipation | 26 | 0
Mucositis [Mucositis includes gingival hypertrophy, gingivitis, gingivitis ulcerative, oral disorder, colitis, mouth ulceration, stomatitis, tongue ulceration, oral pain, oropharyngeal pain, pharyngitis, proctalgia, and colitis ischemic.] | 23 | 3
Diarrhea | 20 | 1
Abdominal pain [Includes multiple similar adverse reaction terms.] | 18 | 1
Vomiting | 17 | 1
General Disorders and Administration Site Conditions
Fatigue/malaise | 36 | 3
Pyrexia | 24 | 1
Edema | 18 | 3
Musculoskeletal and Connective Tissue Disorders
Arthralgia [Arthralgia grouped term includes arthralgia, bone pain, back pain, neck pain, pain in extremity, arthritis, joint effusion, joint range of motion decreased, and joint swelling.] | 28 | 3
Blood System and Lymphatic Disorders
Leukocytosis | 25 | 9
Differentiation syndrome [Includes fatal adverse reaction.] ' [Symptoms of differentiation syndrome in patients treated with REZLIDHIA included leukocytosis, dyspnea, pulmonary infiltrates/pleuropericardial effusion, kidney injury, fever, edema, pyrexia, and weight gain.] | 16 | 8
Respiratory, Thoracic and Mediastinal Disorders
Dyspnea' [Dyspnea grouped term includes acute respiratory distress syndrome, dyspnea, dyspnea exertional, hypoxia, oxygen saturation decreased, respiratory distress, respiratory failure.] | 24 | 5
Cough | 17 | 1
Skin and subcutaneous tissue disorders
Rash | 24 | 1
Investigations
Transaminitis [Transaminitis grouped term includes alanine aminotransferase increased, aspartate aminotransferase increased, hepatic enzyme increased, hypertransaminasemia, liver function test abnormal, liver function test increased, transaminases increased, hepatitis acute, and blood alkaline phosphatase increased.] | 20 | 12
Metabolism and Nutrition Disorders
Decreased appetite | 16 | 2
Nervous System Disorders
Headache | 13 | 0
Vascular Disorders
Hypertension | 10 | 5

Clinically relevant adverse reactions in <10% of patients who received REZLIDHIA include:

- Gallbladder disorders: biliary tract disorder, biliary colic, cholangitis, and cholestasis
- Electrocardiogram QT prolonged

Table 3 summarizes the laboratory abnormalities in the clinical trial for relapsed or refractory AML.

Table 3: Most Common (≥10%) New or Worsening Laboratory Abnormalities in Patients with Relapsed or Refractory AML in the Clinical Trial
 | Olutasidenib [The denominator used to calculate the rate varied from 143 to 152 based on the number of patients with a baseline value and at least one post-treatment value.]
Parameter | All Grades (%) | Grade 3 or 4 (%)
Aspartate aminotransferase increased | 47 | 10
Alanine aminotransferase increased | 46 | 13
Potassium decreased | 46 | 9
Sodium decreased | 42 | 7
Alkaline phosphatase increased | 42 | 7
Creatinine increased | 38 | 2
Lymphocytes increased | 26 | 3
Bilirubin increased | 26 | 2
Uric acid increased | 25 | 3
Lipase increased | 24 | 8

7 DRUG INTERACTIONS

7.1 Effect of Other Drugs on Olutasidenib

Strong or Moderate CYP3A4 Inducers
Avoid concomitant use of REZLIDHIA with strong or moderate CYP3A inducers.

Olutasidenib is a CYP3A substrate. Concomitant use of REZLIDHIA with a strong CYP3A inducer decreases olutasidenib Cmax and AUC, which may reduce REZLIDHIA efficacy [see Clinical Pharmacology (12.3)].

Concomitant use of REZLIDHIA with a moderate CYP3A inducer may also decrease olutasidenib Cmax and AUC, which may also reduce REZLIDHIA efficacy, based on observations from concomitant use with a strong CYP3A inducer.

7.2 Effect of Olutasidenib on Other Drugs

Sensitive CYP3A Substrates

Avoid concomitant use of REZLIDHIA with sensitive CYP3A substrates unless otherwise instructed in the substrates prescribing information. If concomitant use is unavoidable, monitor patients for loss of therapeutic effect of these drugs.

Olutasidenib induces CYP3A. Concomitant use of REZLIDHIA may decrease plasma concentrations of sensitive CYP3A substrates, which may reduce the substrate’s efficacy [see Clinical Pharmacology (12.3)].

8 USE IN SPECIFIC POPULATIONS

8.1 Pregnancy

Risk Summary

Based on animal embryo-fetal toxicity studies, REZLIDHIA may cause fetal harm when administered to a pregnant woman. There are no available data on REZLIDHIA use in pregnant women to evaluate for a drug-associated risk.

In embryo-fetal development studies, oral olutasidenib resulted in embryo-fetal death and altered fetal growth when administered to pregnant rats and rabbits during the period of organogenesis at exposures up to 10 times and 0.7 times, respectively, the human exposure at the recommended daily dose (see Data). Advise pregnant women of the potential risk to a fetus.

In the U.S. general population, the estimated background risk of major birth defects and miscarriage in clinically recognized pregnancies is 2%-4% and 15%-20%, respectively.

Data

Animal Data

Olutasidenib was administered twice daily via oral gavage at dose levels of 25, 125, or 250 mg/kg/dose (50, 250, or 500 mg/kg/day) to pregnant rats during organogenesis (gestation days 6-17). An increase in fetal supernumerary rib was observed at the high dose (10 times the AUC at the clinical dose of 150 mg BID). In a pilot study, administration of olutasidenib orally to pregnant rats during organogenesis resulted in an increase in post-implantation loss at doses of 250 and 450 mg/kg/day (9 and 10 times the AUC at the clinical dose of 150 mg BID).

Olutasidenib was administered twice daily via oral gavage at dose levels of 10, 20, or 40 mg/kg/dose (20, 40, or 80 mg/kg/day) to pregnant rabbits during the period of organogenesis (gestation days 7- 20). Maternal toxicity noted as reduced body weight gain occurred at 80 mg/kg/day. An increase in fetal supernumerary rib and increased post-implantation loss occurred at the high dose of 80 mg/kg/day (0.7 times the AUC at the clinical dose of 150 mg BID).

8.2 Lactation

Risk Summary

There are no data on the presence of olutasidenib or its metabolites in human milk, the effects on the breastfed child, or milk production. Because many drugs are excreted in human milk, and due to the potential for adverse reactions in a breastfed child, advise women not to breastfeed during treatment with REZLIDHIA and for 2 weeks after the last dose.

8.4 Pediatric Use

The safety and effectiveness of REZLIDHIA have not been established in pediatric patients.

8.5 Geriatric Use

Among the 153 patients with relapsed or refractory AML with an IDH1 mutation treated with REZLIDHIA, 116 (76%) were 65 years of age or older and 48 (31%) were 75 years or older. No overall differences in effectiveness were observed between patients 65 years and older and younger patients. Compared to patients younger than 65 years of age, an increase in incidence of hepatotoxicity and hypertension was observed in patients ≥65 years of age.

8.6 Renal Impairment

No dosage modification is recommended for patients with mild to moderate renal impairment (creatinine clearance [CLcr] 30 to <90 mL/min, as estimated by Cockcroft-Gault). The recommended dosage of REZLIDHIA has not been established in patients with severe renal impairment (CLcr 15 to 29 mL/min as estimated by Cockcroft-Gault), kidney failure (CLcr <15 mL/min, as estimated by Cockcroft-Gault), and patients on dialysis [see Clinical Pharmacology (12.3)].

8.7 Hepatic Impairment

No dosage modification is recommended for patients with mild (total bilirubin ≤ULN and any AST >ULN or total bilirubin >1 to 1.5 times ULN and any AST) or moderate (total bilirubin >1.5 to 3 times ULN and any AST) hepatic impairment [see Clinical Pharmacology (12.3)]. In patients with mild or moderate hepatic impairment, closely monitor for increased probability of differentiation syndrome [see Dosage and Administration (2.3) and Warnings and Precautions (5.1)]. The recommended dosage of REZLIDHIA has not been established in patients with severe hepatic impairment (total bilirubin >3 times ULN with any AST) [see Clinical Pharmacology (12.3)].

11 DESCRIPTION

Olutasidenib is an isocitrate dehydrogenase-1 (IDH1) inhibitor. The chemical name is (S)-5-((1-(6-chloro-2-oxo-1,2-dihydroquinolin-3-yl)ethyl)amino)-1-methyl-6-oxo-1,6-dihydropyridine-2-carbonitrile. The chemical structure is:

The molecular formula is C18H15ClN4O2 and the molecular weight is 354.79 g/mol. Olutasidenib is a white to off-white to brown powder that is practically insoluble in aqueous solutions between pH 1.2 and 7.4.

REZLIDHIA (olutasidenib) is available as hard gelatin capsules for oral administration. Each capsule contains 150 mg olutasidenib and the following ingredients: croscarmellose sodium, magnesium stearate and microcrystalline cellulose. The capsule shell contains gelatin and titanium dioxide. Each capsule is printed with black ink containing ferrosoferric oxide, propylene glycol, and shellac.

12 CLINICAL PHARMACOLOGY

12.1 Mechanism of Action

Olutasidenib is a small-molecule inhibitor of mutated isocitrate dehydrogenase-1 (IDH1). In patients with AML, susceptible IDH1 mutations are defined as those leading to increased levels of 2-hydroxyglutarate (2-HG) in the leukemia cells and where efficacy is predicted by 1) clinically meaningful remissions with the recommended dose of olutasidenib and/or 2) inhibition of mutant IDH1 enzymatic activity at concentrations of olutasidenib sustainable at the recommended dosage according to validated methods. The most common of such mutations in patients with AML are R132H and R132C substitutions.

In vitro, olutasidenib inhibited mutated IDH1 R132H, R132L, R132S, R132G, and R132C proteins; wild-type IDH1 or mutated IDH2 proteins were not inhibited. Olutasidenib inhibition of mutant IDH1 led to decreased 2-HG levels in vitro and in in vivo xenograft models.

12.2 Pharmacodynamics

The mean [% coefficient of variation (%CV)] reduction in 2-HG plasma concentration was 59.1% (122%) by pre-dose Cycle 2 and was sustained throughout the treatment period in patients with AML and IDH1 mutations following the approved recommended olutasidenib dosage.

Increased olutasidenib exposure was correlated with the increased probability of differentiation syndrome and Grade ≥3 hepatotoxicity in patients with AML following the approved recommended olutasidenib dosage.

Cardiac Electrophysiology

The largest mean increase in QTc interval was 6.2 msec (upper 90% confidence interval = 9.7 msec) in 33 patients with advanced hematologic malignancies with an IDH1 mutation following a single dose and multiple doses of the approved recommended olutasidenib dosage under fasted conditions. This increase in the QTc interval was concentration dependent.

Increased QT prolongation is expected with increased exposures of olutasidenib under a fed condition compared to that under fasting conditions [see Clinical Pharmacology (12.3)]. The clinical impact of this increase could not be determined because QTc intervals were not evaluated at higher olutasidenib exposures.

12.3 Pharmacokinetics

The pharmacokinetics of olutasidenib have been characterized in patients with AML following the approved recommended dosage, unless otherwise specified.

The mean (%CV) olutasidenib steady-state daily area under the plasma drug concentration over time curve (AUC0-12-h,ss) is 43050 (34.0%) ng·h/mL and steady-state maximum plasma concentration (Cmax,ss) is 3573 (45.6%) ng/mL following the approved recommended dosage.

Olutasidenib Cmax and AUC increase less-than proportionally over a dosage range from 100 mg to 300 mg (0.33 to 1 time the recommended total daily dose); however, this finding should not affect the recommended dosage of REZLIDHIA. Olutasidenib accumulation ratios ranging from 7.7 and 9.5 were observed following the approved recommended dosage. Steady-state plasma levels are reached within 14 days.

Absorption

The median (min, max) time to maximum concentration (tmax) of olutasidenib is approximately 4 (1, 8) hours following a single oral dose of 150 mg.

Effect of Food

The mean (CV%) of olutasidenib Cmax increased by 191% (20.6%) and AUCinf increased by 83% (18.3%) following administration of a single 150 mg dose of olutasidenib with a high-fat meal (approximately 800 to 1,000 calories, with approximately 50% of total caloric content of the meal from fat) in healthy subjects.

Distribution

The mean (CV%) apparent volume of distribution of olutasidenib is 319 (28.1%) L. The plasma protein binding of olutasidenib is approximately 93%.

Elimination

The mean (CV%) half-life (t1⁄2) of olutasidenib is approximately 67 (51.2%) hours and the mean (CV%) apparent oral clearance (CL/F) of olutasidenib is 4 (60.5%) L/h.

Metabolism

Olutasidenib metabolism involves N-dealkylation, demethylation, oxidative deamination followed by oxidation, mono-oxidation with subsequent glucuronidation. Olutasidenib is primarily (90%) metabolized by cytochrome P450(CYP)3A4, with minor contributions from CYP2C8, CYP2C9, CYP1A2, and CYP2C19.

Excretion

Following a single oral radiolabeled olutasidenib dose of 150 mg to healthy subjects, approximately 75% of olutasidenib was recovered in feces (35% unchanged) and 17% in the urine (1% unchanged).

Specific Populations

No clinically significant differences in the pharmacokinetics of olutasidenib were observed based on age (28 to 90 years), sex, body weight (36 to 145 kg), mild to moderate renal impairment (creatinine clearance [CLcr] 30 to <90mL/min as estimated by Cockcroft-Gault), or mild (total bilirubin ≤ULN and any AST >ULN or total bilirubin >1 to 1.5 times ULN and any AST) or moderate (total bilirubin >1.5 to 3 times ULN and any AST) hepatic impairment.

The effect of severe renal impairment (CLcr 15 to 29 mL/min, as estimated by Cockcroft-Gault), kidney failure (CLcr <15 mL/min, as estimated by Cockcroft-Gault), patients on dialysis, and patients with severe hepatic impairment (total bilirubin >3 x ULN with any AST) on olutasidenib pharmacokinetics is unknown or not fully characterized.

Drug Interaction Studies

Clinical Studies

Strong CYP3A and P-glycoprotein (P-gp) Inhibitors: No clinically significant differences in olutasidenib pharmacokinetics were observed when used concomitantly with multiple doses of a strong CYP3A and P-gp inhibitor (itraconazole).

Strong CYP3A4 Inducers: Olutasidenib Cmax decreased by 43% and AUC by 80% when used concomitantly with multiple doses of a strong CYP3A inducer (rifampin).

In vitro Studies

CYP Enzymes: Olutasidenib induces CYP3A4, CYP2B6, CYP1A2, CYP2C8 and CYP2C9.

Olutasidenib does not inhibit CYP1A2, CYP2B6, CYP2C8, CYP2C9, CYP2C19, CYP2D6, and CYP3A4/5.

Transporter Systems: Olutasidenib is not a substrate of BCRP, BSEP, MRP2, MRP3, or MRP4.

Ivosidenib does not inhibit BCRP, OATP1B1, OATP1B3, OAT1, and OCT2 at clinically relevant concentrations. Ivosidenib is an inhibitor of OAT3 and P-gp.

Olutasidenib is an inhibitor of P-gp, BCRP, OATP1B1, OATP1B3, OAT3, OCT2, MATE1, and MATE2K. Olutasidenib does not inhibit BSEP, MRP2, MRP3, MRP4, or OAT1.

13 NONCLINICAL TOXICOLOGY

13.1 Carcinogenesis, Mutagenesis, Impairment of Fertility

Carcinogenicity studies have not been conducted with olutasidenib. Olutasidenib was not genotoxic in the in vitro bacterial reverse mutation (Ames), in vitro human lymphocyte micronucleus, and in vivo rat bone marrow micronucleus assays. Fertility studies in animals have not been conducted with olutasidenib.

13.2 Animal Toxicology and/or Pharmacology

Olutasidenib was phototoxic in vitro and in vivo. In pigmented rats, oral administration of olutasidenib for 3 consecutive days followed by exposure to UV light 2 hours after the last dose resulted in skin erythema which persisted for 72 hours.

14 CLINICAL STUDIES

14.1 Acute Myeloid Leukemia

The efficacy of REZLIDHIA was evaluated in an open-label, single-arm, multicenter clinical trial (Study 2102-HEM-101, NCT02719574) in 147 adult patients with relapsed or refractory AML with an IDH1 mutation.

IDH1 mutations in blood or bone marrow were confirmed retrospectively using the Abbott RealTime™ IDH1 Assay. REZLIDHIA was given orally at a dose of 150 mg twice daily until disease progression, development of unacceptable toxicity, or hematopoietic stem cell transplantation. Sixteen of the 147 patients (11%) underwent stem cell transplantation following REZLIDHIA treatment.

The baseline demographic and disease characteristics are shown in Table 4.

Table 4: Baseline Demographic and Disease Characteristics in Patients with Relapsed or Refractory AML (Study 2102-HEM-101)
Demographic and Disease Characteristics | REZLIDHIA (150 mg twice daily) N=147
Demographics
Age (Years) Median (Min, Max) | 71 (32, 87)
Age Categories, n (%)
<65 years | 37 (25)
≥65 years to <75 years | 65 (44)
≥75 years | 45 (31)
Sex, n (%)
Male | 74 (50)
Female | 73 (50)
Race, n (%)
White | 67 (46)
Black or African American | 5 (3)
Asian | 5 (3)
Native Hawaiian/Other Pacific Islander | 0 (0)
Other/Not provided | 70 (48)
Disease Characteristics
ECOG PS, n (%)
0 | 45 (31)
1 | 76 (52)
2 | 23 (16)
IDH1 Mutation, n (%) [Using central IDH1 assay testing results.]
R132C | 85 (58)
R132H | 35 (24)
R132G | 12 (8)
R132S | 11 (7)
R132L | 4 (3)
Type of AML, n (%)
De novo AML | 97 (66)
Secondary AML | 50 (34)
Cytogenetic Risk Status [Cytogenetic risk categorization was investigator reported by NCCN or ELN guidelines.] , n (%)
Favorable | 6 (4)
Intermediate | 107 (73)
Poor | 25 (17)
Unknown | 9 (6)
Relapsed/Refractory Patient Category
Primary Refractory | 46 (31)
Untreated Relapse [May be first or subsequent relapse.] | 81 (55)
Refractory Relapse | 20 (14)
Relapse Number
0 | 46 (31)
1 | 87 (59)
2 | 11 (8)
≥3 | 3 (2)
Prior Stem Cell Transplantation for AML, n (%) | 17 (12)
Transfusion Dependent at Baseline [Transfusion-Dependent at Baseline is defined as receiving a transfusion within 8 weeks prior to first dose of olutasidenib or noting transfusion dependence prior to coming on study.] , n (%) | 86 (59)
Median Number of Prior Therapies (Min, Max) | 2 (1,7)

Efficacy was established on the basis of the rate of complete remission (CR) plus complete remission with partial hematologic recovery (CRh), the duration of CR+CRh, and the rate of conversion from transfusion dependence to transfusion independence. The efficacy results are shown in Table 5. The median follow-up was 10.2 months (range: 0.2 to 38.1 months) and median treatment duration was 4.7 months (range: 0.1 to 26.0 months).

Table 5: Efficacy Results in Patients with Relapsed or Refractory AML (Study 2102-HEM-101)
Endpoint | REZLIDHIA (150 mg twice daily) N=147
CR+CRh [CR (complete remission) was defined as <5% blasts in the bone marrow, no blasts with Auer rods, no extramedullary disease, and full recovery of peripheral blood counts (platelets >100,000/microliter and absolute neutrophil counts [ANC] >1,000/microliter); CRh (complete remission with partial hematologic recovery) was defined as <5% blasts in the bone marrow, no evidence of disease, and partial recovery of peripheral blood counts (platelets >50,000/microliter and ANC >500/microliter).] , [CR+CRh rate was consistent across all baseline demographic and baseline disease characteristic subgroups with the exception of IDH1 R132H mutation (CR+CRh 17%).] n (%) | 51 (35)
95% CI | (27, 43)
Median DOCR+CRh [Duration of response is defined as the time from the date of the first response to the date of the relapse or death. Patients who did not relapse were censored at the date of last response assessment. + indicates censored observation.] (months) | 25.9
95% CI | (13.5, NR)
CR n (%) | 47 (32)
95% CI | (25, 40)
Median DOCR (months) | 28.1
95% CI | (13.8, NR)
CRh n (%) | 4 (2.7)
95% CI | (0.7, 6.8)
Observed DOCRh (months) | 1.8, 5.6, 13.5, 28.5+
CI: confidence interval; NR = not reached

Of the patients who achieved a CR or CRh, the median time to CR or CRh was 1.9 months (range: 0.9 to 5.6 months). All patients that achieved a best response of CR or CRh did so within 5.6 months of initiating REZLIDHIA.

Overall, among the 86 patients who were dependent on red blood cell (RBC) and/or platelet transfusions at baseline, 29 (34%) became independent of RBC and platelet transfusions during any 56-day post-baseline period. Of the 61 patients who were independent of both RBC and platelet transfusions at baseline, 39 (64%) remained transfusion independent during any 56-day post- baseline period.

16 HOW SUPPLIED/STORAGE AND HANDLING

How Supplied

Capsule Strength | Description | Package Configuration | NDC Number
150 mg | White hard gelatin capsules with black ink print "OLU 150" | White high-density polyethylene (HDPE) bottle with child-resistant closure | 71332-005-01
 |  | Each bottle contains 30 capsules

Storage

Store at 20°C to 25°C (68°F to 77°F); excursions permitted between 15°C and 30°C (59°F and 86°F)
[see USP Controlled Room Temperature].

17 PATIENT COUNSELING INFORMATION

Advise the patient to read the FDA-approved patient labeling (Medication Guide).

Differentiation Syndrome

Advise patients of the risks of developing differentiation syndrome as early as 1 day after start of therapy and up to 18 months on treatment. Ask patients to immediately report any symptoms suggestive of differentiation syndrome, such as fever, cough or difficulty breathing, decreased urinary output, low blood pressure, weight gain, or swelling of their arms or legs, to their healthcare provider for further evaluation [see Warnings and Precautions (5.1)].

Hepatotoxicity

Advise patients of the potential for hepatic effects and to immediately report any associated signs and symptoms such as right upper abdominal discomfort, dark urine, jaundice, anorexia, or fatigue to their healthcare provider for further evaluation [see Warnings and Precautions (5.2)].

Gastrointestinal Adverse Reactions

Advise patients on the risks of experiencing gastrointestinal reactions such as nausea, constipation, diarrhea, vomiting, abdominal pain, and mucositis. Ask patients to report these events to their healthcare provider and advise patients how to manage them [see Adverse Reactions (6.1)].

Lactation

Advise women not to breastfeed during treatment with REZLIDHIA and for 2 weeks after the last dose [see Use in Specific Populations (8.2)].

Dosing and Storage Instructions

- Advise patients to swallow capsules whole. Do not break, open, or chew the capsules.
- Advise patients to take REZLIDHIA on an empty stomach (at least 1 hour before or 2 hours after a meal).
- Advise patients that if a dose of REZLIDHIA is vomited, do not administer a replacement dose; wait until the next scheduled dose is due.
- If a dose of REZLIDHIA is missed or not taken at the usual time, instruct patients to take the dose as soon as possible unless the next dose is due within 8 hours. Patients can return to the normal schedule the following day.
- Store REZLIDHIA at room temperature from 20°C to 25°C (68°F to 77°F).

Manufactured by Catalent Greenville, Inc. 1240 Sugg Pkwy, Greenville, NC 27834
Manufactured for Rigel Pharmaceuticals, Inc. South San Francisco, CA 94080

REZLIDHIA® is a trademark of Rigel Pharmaceuticals, Inc.
For more information go to www.REZLIDHIA.com or call 1-800-983-1329.

04/2024

MEDICATION GUIDE

REZLIDHIA® (REZ-LID-EE-AH)
(olutasidenib) capsules

What is the most important information I should know about REZLIDHIA?

REZLIDHIA may cause serious side effects including:

- Differentiation Syndrome. Differentiation syndrome is a condition that affects your blood cells and may be life- threatening or lead to death. Differentiation syndrome in adults with acute myeloid leukemia (AML) has occurred as early as 1 day and up to 18 months after starting REZLIDHIA. Call your healthcare provider or go to the nearest hospital emergency room right away if you develop any of the following symptoms of differentiation syndrome during treatment with REZLIDHIA:
  - fever
  - cough
  - trouble breathing
  - decreased urination
  - dizziness or lightheadedness
  - weight gain
  - swelling of your arms or legs

If you develop signs and symptoms of differentiation syndrome, your healthcare provider may treat you with a corticosteroid medicine or a medicine called hydroxyurea and may monitor you in the hospital.

See "What are the possible side effects of REZLIDHIA?" for more information about side effects.

What is REZLIDHIA?

REZLIDHIA is a prescription medicine used to treat adults with acute myeloid leukemia (AML) with an isocitrate dehydrogenase-1 (IDH1) mutation when the disease has come back or has not improved after previous treatment(s).

Your healthcare provider will perform a test to make sure that REZLIDHIA is right for you.

It is not known if REZLIDHIA is safe and effective in children.

Before taking REZLIDHIA, tell your healthcare provider about all of your medical conditions, including if you:

- have liver problems.
- are pregnant or plan to become pregnant. REZLIDHIA may harm your unborn baby.
- are breastfeeding or plan to breastfeed. It is not known if REZLIDHIA passes into your breast milk. Do not breastfeed during your treatment with REZLIDHIA and for 2 weeks after your last dose of REZLIDHIA.

Tell your healthcare provider about all the medicines you take, including prescription and over-the-counter medicines, vitamins, and herbal supplements.

How should I take REZLIDHIA?

- Take REZLIDHIA exactly as your healthcare provider tells you to.
- Do not change your dose or stop taking REZLIDHIA without talking to your healthcare provider.
- Take REZLIDHIA 2 times a day (about 12 hours apart) around the same times each day.
- Take REZLIDHIA on an empty stomach, at least 1 hour before or 2 hours after a meal.
- Swallow REZLIDHIA capsules whole. Do not break, open or chew the capsules.
- If you vomit after taking a dose of REZLIDHIA, do not take another dose. Take your next dose at your usual time.
- If you miss a dose of REZLIDHIA or did not take it at the usual time, take your dose as soon as possible and at least 8 hours before your next dose. Return to your normal schedule the following day. Do not take 2 doses of REZLIDHIA within 8 hours.

What are the possible side effects of REZLIDHIA?

REZLIDHIA may cause serious side effects, including:

- See “What is the most important information I should know about REZLIDHIA?”
- Liver problems. Changes in liver function tests are common during treatment with REZLIDHIA and can be serious. Your healthcare provider will do blood tests to check your liver function before and during treatment with REZLIDHIA. Tell your healthcare provider right away if you develop any of the following symptoms of liver problems during treatment with REZLIDHIA:
  - yellowing of your skin or the white part of your eyes (jaundice)
  - dark “tea-colored” urine
  - loss of appetite
  - pain on the upper right side of your stomach area
  - feeling very tired or weak

The most common side effects of REZLIDHIA in adults with AML include:

- abnormal liver function tests
- nausea
- feeling tired or unwell
- joint pain
- constipation
- shortness of breath
- fever
- rash
- mouth sores
- diarrhea
- changes in certain blood tests

Tell your healthcare provider if you have any nausea, constipation, diarrhea, vomiting, stomach pain or mouth sores.

Your healthcare provider will do blood tests before you start and during treatment with REZLIDHIA. Your healthcare provider may decrease, temporarily hold, or permanently stop your treatment with REZLIDHIA if you develop certain side effects.

These are not all the possible side effects of REZLIDHIA.

Call your doctor for medical advice about side effects. You may report side effects to FDA at 1-800-FDA-1088.

How should I store REZLIDHIA?

Store REZLIDHIA at room temperature from 68°F to 77°F (20°C to 25°C).

Keep REZLIDHIA and all medicines out of the reach of children.

General information about the safe and effective use of REZLIDHIA

Medicines are sometimes prescribed for purposes other than those listed in a Medication Guide. Do not take REZLIDHIA for conditions for which it was not prescribed. Do not give REZLIDHIA to other people, even if they have the same symptoms you have. It may harm them. You can ask your pharmacist or healthcare provider for information about REZLIDHIA that is written for healthcare professionals.

What are the ingredients in REZLIDHIA?

Active ingredient: olutasidenib

Inactive ingredients:
croscarmellose sodium, magnesium stearate, and microcrystalline cellulose. The capsule shell contains gelatin and titanium dioxide. Each capsule is printed with black ink containing ferrosoferric oxide, propylene glycol and shellac.

Manufactured by Catalent Greenville, Inc. 1240 Sugg Pkwy, Greenville, NC 27834
Manufactured for Rigel Pharmaceuticals, Inc. South San Francisco, CA 94080
REZLIDHIA® is a trademark of Rigel Pharmaceuticals, Inc.
For more information go to www.REZLIDHIA.com or call 1-800-983-1329.

This Medication Guide has been approved by the U.S. Food and Drug Administration.

Issued: 04/2024

PRINCIPAL DISPLAY PANEL - REZLIDHIA - NDC 71332-005-01 - 150 mg Capsule 30-Count Carton Label

NDC: 71332-005-01

Rx only

REZLIDHIA®

olutasidenib capsules

150 mg

Dispense the enclosed Medication Guide to each patient.

30 capsules